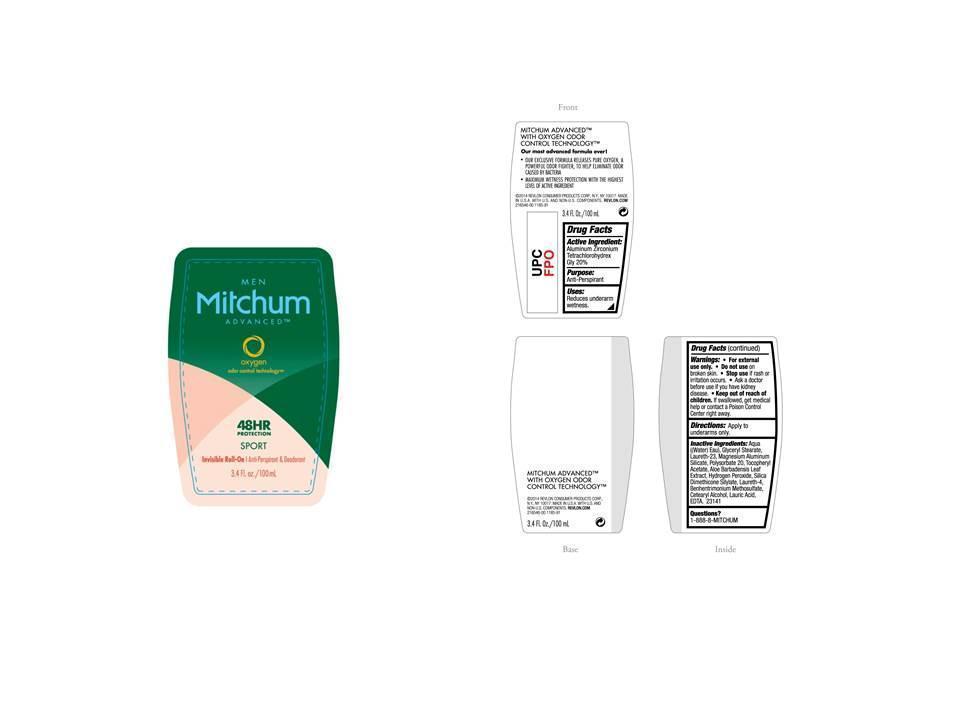 DRUG LABEL: Mens Mitchum Advanced Invisible
NDC: 10967-584 | Form: LIQUID
Manufacturer: Revlon Consumer Products Corp
Category: otc | Type: HUMAN OTC DRUG LABEL
Date: 20131210

ACTIVE INGREDIENTS: ALUMINUM ZIRCONIUM TETRACHLOROHYDREX GLY 0.20 g/1 mL
INACTIVE INGREDIENTS: WATER; GLYCERYL MONOSTEARATE; LAURETH-23; MAGNESIUM ALUMINUM SILICATE; POLYSORBATE 20; .ALPHA.-TOCOPHEROL ACETATE; ALOE VERA LEAF; HYDROGEN PEROXIDE; SILICA DIMETHYL SILYLATE; LAURETH-4; BEHENTRIMONIUM METHOSULFATE; CETOSTEARYL ALCOHOL; LAURIC ACID; EDETIC ACID; LINALOOL, (+)-; .BETA.-CITRONELLOL, (R)-

Mens Mitchum Advanced Roll On Antiperspirant Deodorant - Sport 3.4 fl.oz

Drug Facts Active Ingredient

Aluminum zirconium tetrachlorohydrex gly 20%

Purpose

Antiperspirant

Use

- Reduces underarm wetness

Warnings:

For external use only.

Do not use on broken skin

Ask a doctor before use if you have kidney disease

Stop use if rash or irriation occurs

Keep out of reach of children.

If swallowed, get medical help or contact a Poison Control Center right away.

Directions

Apply to underarms only.

Inactive Ingredients

aqua((water) eau), glyceryl stearate, laureth-23, magnesium aluminum silicate, polysorbate 20, tocopheryl acetate, aloe barbadensis leaf extract, hydrogen peroxide, silica dimethicone silylate, laureth-4, behentrimonium methosulfate, cetearyl alcohol, lauric acid, EDTA, parfum(fragrance), Linalool, Citronellol

Questions

1-888-8-MITCHUM